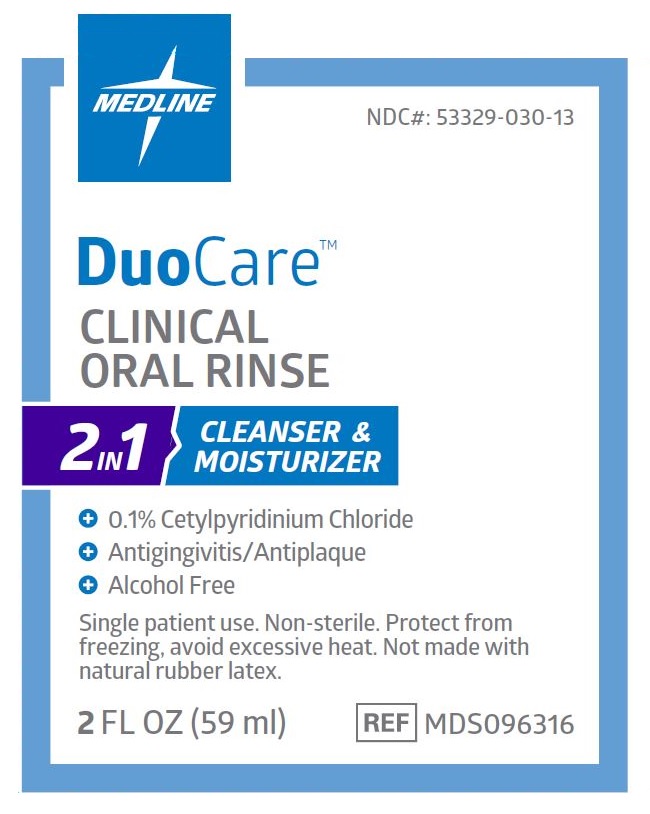 DRUG LABEL: DuoCare Clinical Oral Rinse
NDC: 53329-030 | Form: MOUTHWASH
Manufacturer: Medline Industries, LP
Category: otc | Type: HUMAN OTC DRUG LABEL
Date: 20231016

ACTIVE INGREDIENTS: CETYLPYRIDINIUM CHLORIDE 1 mg/1 mL
INACTIVE INGREDIENTS: SUCRALOSE; CITRIC ACID MONOHYDRATE; POLOXAMER 407; GLYCERIN; METHYL SALICYLATE; SODIUM CITRATE; WATER

030 DuoCare™ Clinical Oral Rinse

Active ingredient

Cetylpyridinium Chloride 0.1%

Purpose

Antigingivitis/Antiplaque

Uses

- helps prevent and reduce plaque that leads to gingivitis and bleeding gums

Warnings

Stop use and ask a doctor if

- gingivitis, bleeding, or redness persists for more than 2 weeks
- you have painful or swollen gums, pus from the gum line, loose teeth, or increasingspacing between the teeth. These may be signs or symptoms of periodontitis, a serious form of gum disease.

Keep out of reach of children.

If more than used for rinsing is accidentally swallowed, get medical help or contact a Poison Control Center right away.

Directions

- adults and children 12 years of age and older: swish 7 ml of rinse between your teeth for approximately one minute and then spit out. Do not swallow the rinse.
- Use up to 4 times daily or as directed by dentist or doctor.
- children 6 years to under 12 years of age: supervise use.
- children under 6 years of age: consult a dentist or a doctor.

Other information

- avoid excessive heat and protect from freezing
- shield from direct sunlight

Inactive ingredients

citric acid, glycerin, methyl salicylate, poloxamer 407, purified water, sodium citrate, sucralose, supermint

Manufacturing Information

Manufactured for:

Medline Industries, LP

Three Lakes Drive, Northﬁeld, IL 60093 USA

Made in the USA with U.S. and Foreign Components.

www.medline.com

1-800-MEDLINE (633-5463)

REF: MDS096316

V1 RC22ANO

RECENT MAJOR CHANGES

- Dosage and Administration